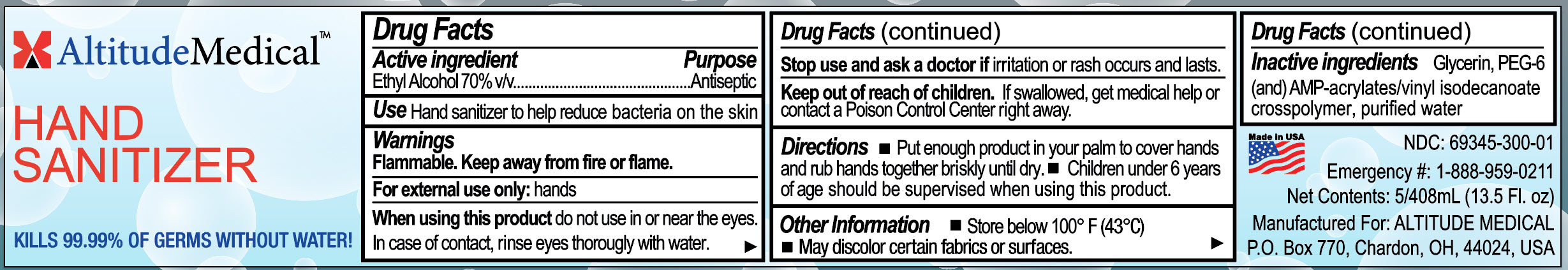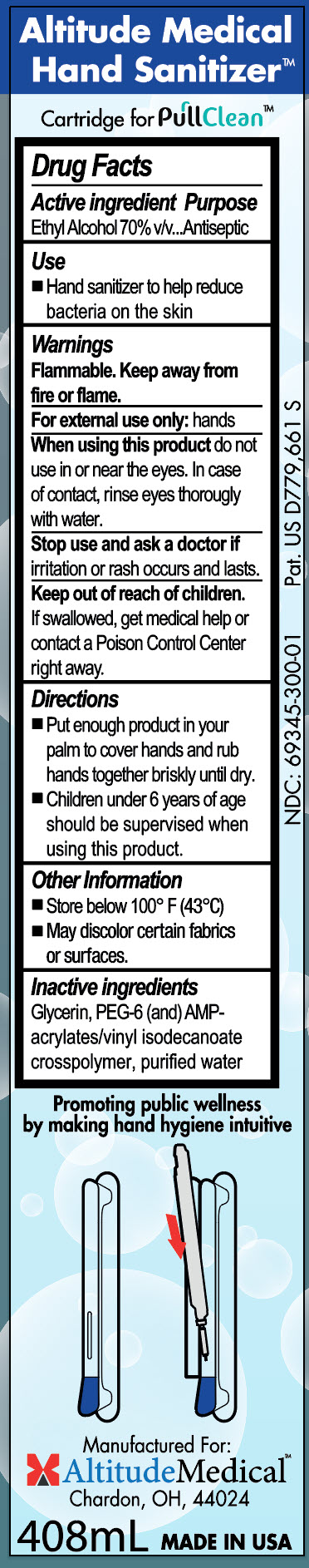 DRUG LABEL: Altitude Medical Hand Sanitizer
NDC: 69345-300 | Form: GEL, METERED
Manufacturer: Altitude Medical
Category: otc | Type: HUMAN OTC DRUG LABEL
Date: 20220103

ACTIVE INGREDIENTS: ALCOHOL 70 mL/100 mL
INACTIVE INGREDIENTS: ISOPROPYL ALCOHOL; RAPIDGEL EZ1; WATER; GLYCERIN

Altitude Medical - PullClean Hand Sanitizer

ACTIVE INGREDIENT

Ethyl alcohol …….. 70% v/v

PURPOSE

Antiseptic

USE

Hand sanitizer to help reduce bacteria on the skin

WARNINGS

Flammable. Keep away from heat or flame.

For external use only: hands

WHEN USING

When using this product do not use in or near eyes.

In case of contact, rinse eyes thoroughly with water.

STOP USE

Stop use and ask a doctor if irritation or rash occurs and lasts.

Keep out of reach of children. If swallowed, get medical help, or contact a Poison Control Center right away.

DIRECTIONS

• Place enough product in your palm to cover hands and rub hands together briskly until dry.

• Children under 6 years of age should be supervised when using this product.

OTHER INFORMATION

• Store below 100°F (43°C)

• May discolor certain fabrics or surfaces.

INACTIVE INGREDIENTS

Glycerin, isopropyl alcohol, PEG-6 (and) AMP-acrylates/vinyl isodecanoate crosspolymer, purified water